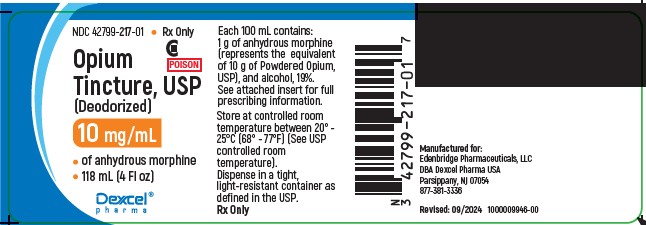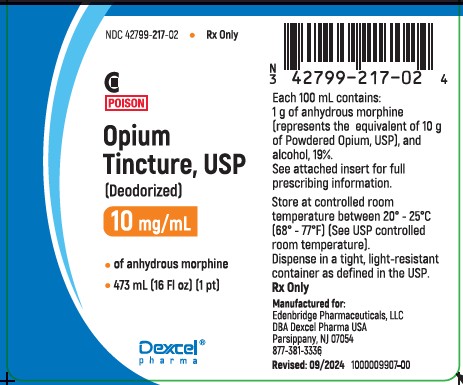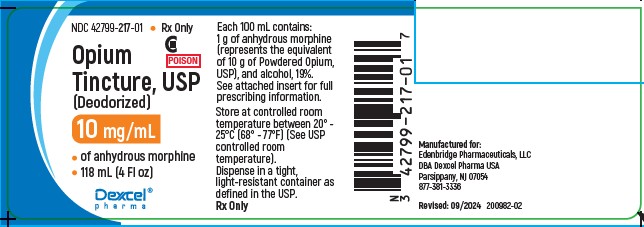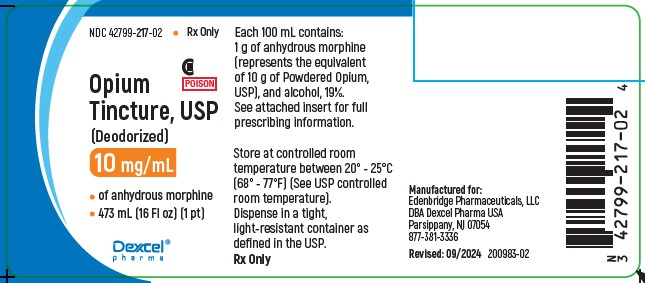 DRUG LABEL: Opium Tincture Deodorized
NDC: 42799-217 | Form: TINCTURE
Manufacturer: Edenbridge Pharmaceuticals, LLC
Category: prescription | Type: HUMAN PRESCRIPTION DRUG LABEL
Date: 20251226
DEA Schedule: CII

ACTIVE INGREDIENTS: MORPHINE 10 mg/1 mL
INACTIVE INGREDIENTS: ALCOHOL

OPIUM TINCTURE, USP (DEODORIZED) CII Rx only

DESCRIPTION

Opium Tincture, USP (Deodorized), is for oral administration. It is freed from unpleasant odor or nauseating substances by “denarcotization” with a petroleum distillate. Opium tincture is a clear, reddish-brown hydroalcoholic solution.

Each 100 mL contains 1 g of anhydrous morphine (represents the equivalent of 10 g of Powdered Opium, USP), alcohol, 19%, and water.

Opium has a very characteristic odor and a very bitter taste. The opiates are the most effective and prompt-acting nonspecific antidiarrheal agents.

CLINICAL PHARMACOLOGY

The opiates act by enhancing tone in the long segments of longitudinal muscle and by inhibiting propulsive contraction of both circular and longitudinal muscles.

Clinical evidence indicates that the analgesic activity of opium preparations is due to their morphine content. Relatively small doses that do not produce significant analgesia are effective in controlling diarrhea. The papaverine content of the mixed alkaloids is too small to have demonstrable spasmolytic activity.

Following oral administration, morphine is well absorbed from the gastrointestinal tract. It is rapidly metabolized following oral administration, however, and plasma levels of unconjugated morphine are lower than those achieved after parenteral administration. Like other narcotic analgesics, opium preparations are metabolized in the liver. Morphine undergoes conjugation with glucuronic acid at the 3-hydroxyl group. Secondary conjugation may also occur at the 6-hydroxyl group to form the 3,6-diglucuronide. Morphine is excreted in the urine mainly as morphine-3-glucuronide and smaller amounts of morphine-3,6-diglucuronide and unchanged drug. Approximately 75% of a dose of morphine is excreted in the urine within 48 hours.

INDICATIONS AND USAGE

Opium tincture is useful for the treatment of diarrhea.

CONTRAINDICATIONS

This preparation is not recommended for use in children. It should not be used in diarrhea caused by poisoning until the toxic material is eliminated from the gastrointestinal tract.

WARNINGS

Addiction can result from opium usage. Opium preparations should be given in the smallest effective dose and as infrequently as possible to minimize the development of tolerance and physical dependence.

PRECAUTIONS

General– Opium should be used with caution in the elderly, in debilitated individuals, and in patients with increased intracranial pressure, cerebral arteriosclerosis, hepatic cirrhosis or liver insufficiency, gastrointestinal hemorrhage, myxedema, emphysema, and bronchial asthma.

Drug Interactions– When preparations containing opium are administered in combination with other drugs, the cautions applicable to each ingredient should be borne in mind. Reduced dosage is indicated in poor-risk patients, in the very young or very old patient, and in those who are receiving other central-nervous system depressants.

Usage in Pregnancy - Pregnancy Category C– Animal reproduction studies have not been conducted with Opium Tincture USP (Deodorized). It is also not known whether Opium Tincture, USP (Deodorized), can cause fetal harm when administered to a pregnant woman or can affect reproduction capacity. Opium Tincture, USP (Deodorized), should be given to a pregnant woman only if clearly needed.

Nursing Mothers– Caution should be exercised when Opium Tincture, USP (Deodorized), is administered to a nursing woman.

Usage in Children– Safety and effectiveness in children have not been established. See CONTRAINDICATIONS.

ADVERSE REACTIONS

Constipation, nausea, and vomiting may occur in some patients. Pruritus and urticaria have been observed.

DRUG ABUSE AND DEPENDENCE

Controlled Substance– Opium Tincture, USP (Deodorized), is a Schedule II drug. See WARNINGS.

OVERDOSAGE

Signs and Symptoms– Symptoms of toxicity are those of morphine and alcohol, such as nausea, vomiting, miosis, cool and clammy skin, respiratory and CNS depression, bradycardia, hypotension, and skeletal muscle flaccidity. Noncardiogenic pulmonary edema may develop after opioid overdose and monitoring of heart filling pressure may be helpful. Ethanol has been demonstrated to cause hypoglycemia in children or adults with limited glycogen stores. In severe overdosage, apnea, circulatory collapse, cardiac arrest, and death may occur.

Treatment– To obtain up-to-date information about the treatment of overdose, a good resource is your certified Regional Poison Control Center. Telephone numbers of certified poison control centers are listed in the Physicians’ Desk Reference (PDR). In managing overdosage, consider the possibility of multiple drug overdoses, interaction among drugs, and unusual drug kinetics in your patient.

Initial management of opioid overdose should emphasize establishment of a secure airway and support of ventilation and perfusion. Meticulously monitor and maintain, within acceptable limits, the patient’s vital signs, blood gases, serum electrolytes, blood glucose, etc. Naloxone antagonizes most effects of opioids. Protect the airway as naloxone may induce vomiting. Since naloxone has a shorter duration of action than opioids, repeated doses may be needed. In patients who abuse opioids chronically, a withdrawal syndrome may be manifest on administration of naloxone. This may include yawning, tearing, restlessness, sweating, dilated pupils, piloerection, vomiting, diarrhea, and abdominal cramps. This syndrome usually abates quickly as the effect of naloxone dissipates.

Absorption of drugs from the gastrointestinal tract may be decreased by giving activated charcoal, which, in many cases, is more effective than emesis or lavage; consider charcoal instead of or in addition to gastric emptying. Repeated doses of charcoal over time may hasten elimination of some drugs that have been absorbed. Since opium tincture can delay gastric emptying, evacuation of the stomach may be beneficial. Safeguard the patient’s airway when employing gastric emptying or charcoal. Monitor for and treat hypoglycemia.

The use of forced diuresis, peritoneal dialysis, hemodialysis or charcoal hemoperfusion has not been established to be beneficial.

DOSAGE AND ADMINISTRATION

Usual Adult Dose– 0.6 mL orally 4 times a day.

HOW SUPPLIED

Opium Tincture, USP (Deodorized), is supplied as:
NDC 42799-217-01 Bottles of 4 fl oz
NDC 42799-217-02 Bottles of 16 fl oz

Store at controlled room temperature, 68° to 77°F (20° to 25°C) (see USP).

Manufactured for:
Edenbridge Pharmaceuticals, LLC
DBA Dexcel Pharma USA

Parsippany, NJ 07054 USA

877-381-3336
Rev. 09/2024
1000009908-00